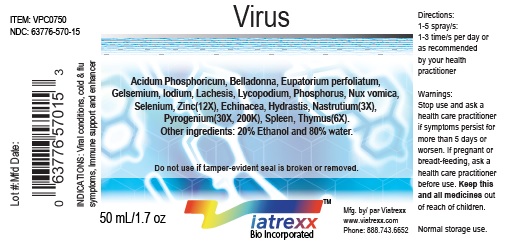 DRUG LABEL: Viatrexx-Virus
NDC: 63776-570 | Form: SPRAY
Manufacturer: VIATREXX BIO INCORPORATED
Category: homeopathic | Type: HUMAN OTC DRUG LABEL
Date: 20190319

ACTIVE INGREDIENTS: Phosphoric Acid 12 [kp_C]/1 mL; Atropa Belladonna 12 [kp_C]/1 mL; Echinacea Angustifolia 3 [kp_C]/1 mL; Eupatorium Perfoliatum Whole 12 [kp_C]/1 mL; Gelsemium Sempervirens Root 12 [kp_C]/1 mL; Goldenseal 3 [kp_C]/1 mL; Iodine 12 [kp_C]/1 mL; Lachesis Muta Venom 12 [kp_C]/1 mL; Lycopodium Clavatum Spore 12 [kp_C]/1 mL; Tropaeolum Majus 3 [kp_C]/1 mL; Strychnos Nux-Vomica Seed 12 [kp_C]/1 mL; Phosphorus 12 [kp_C]/1 mL; Rancid Beef 30 [kp_C]/1 mL; Selenium 12 [kp_C]/1 mL; Sus Scrofa Spleen 6 [kp_C]/1 mL; Bos Taurus Spleen 6 [kp_C]/1 mL; Sus Scrofa Thymus 6 [kp_C]/1 mL; Bos Taurus Thymus 6 [kp_C]/1 mL; Zinc 12 [kp_C]/1 mL
INACTIVE INGREDIENTS: Alcohol; Water

Virus

Active Ingredients

Acidum phosphoricum (12X), Belladonna (12X), Echinacea (3X), Eupatorium perfoliatum (12X), Gelsemium (12X), Hydrastis (3X), Iodium (12X), Lachesis (12X), Lycopodium (12X), Nastrutium (3X), Nux Vomica (12X), Phosphorus (12X), Pyrogenium (30X, 200K), Selenium (12X), Spleen (6X), Thymus (6X), Zinc (12X).

Purpose

Acidum phosphoricum
Belladonna
Echinacea
Eupatorium perfoliatum
Gelsemium
Hydrastis
Iodium
Lachesis
Lycopodium
Nastrutium
Nux Vomica
Phosphorus
Pyrogenium
Selenium
Spleen
Thymus
Zinc

Immune support
Drainage
Immune support
Drainage
Neurological support
Drainage
Thyroid support
Anti-inflammation
Drainage
Drainage
Drainage
Drainage
Drainage
Nutritional Support
Regeneration
Immune support
Neurological support

Description

Viatrexx-Virus is a homeopathic product composed of physiological (low dose and low low dose) natural micro nutrients. These micro particles are designed to nourish the system.

Uses

Viral conditions, cold and flu symptoms, Immune support and enhancer.

Dosage

1-3 spray(s); 1-3 time(s) per day or as recommended by your health care practitioner.

Warnings

Stop use and ask a health care practitioner if symptoms persist for more than 5 days or worsen. If pregnant or breastfeeding, ask a health care practitioner before use.

Inactive Ingredients

20% Alcohol and 80% Water.

Product availability

Product may be acquired in 0.5, 30 ,50, 100, 250 mL bottles.

References upon request

To report SUSPECTED ADVERSE REACTIONS, contact the FDA at 1-800-FDA-1088 or www.fda.gov/medwatch

Distributed by
Viatrexx Bio Incorporated
Newark, DE, USA, 19713

Manufactured by
8046255 Canada Inc
Beloeil, Qc, J3G 6S3
Date of last revision March 2019

For Questions and comments
Info@Viatrexx.com
www.Viatrexx.com

PACKAGE LABEL.PRINCIPAL DISPLAY PANEL

NDC: 63776-570-11
Item: VPC0750
Viatrexx Bio Incorporated
Viatrexx-Virus
Box of 1 X 0.5 mL ampule
For Oral and Topical Use
Expiry date: Lot #:
Manufactured for:
Viatrexx Bio Incorporated Newark, DE, USA, 19713
www.Viatrexx.com
Ingredients, homeopathic
See insert or www.viatrexx.com
Inactives: Alcohol 20%, Water 80%

NDC: 63776-570-14
Item: VPC0750
Viatrexx Bio Incorporated
Viatrexx-Virus
Box of 1 X 30 mL spray bottle
For Oral and Topical Use
Expiry date: Lot #:
Manufactured for:
Viatrexx Bio Incorporated Newark, DE, USA, 19713
www.Viatrexx.com
Ingredients, homeopathic
See insert or www.viatrexx.com
Inactives: Alcohol 20%, Water 80%

NDC: 63776-570-15
Item: VPC0750
Viatrexx Bio Incorporated
Viatrexx-Virus
Box of 1 X 50 mL spray bottle
For Oral and Topical Use
Expiry date: Lot #:
Manufactured for:
Viatrexx Bio Incorporated Newark, DE, USA, 19713
www.Viatrexx.com
Ingredients, homeopathic
See insert or www.viatrexx.com
Inactives: Alcohol 20%, Water 80%

NDC: 63776-570-16
Item: VPC0750
Viatrexx Bio Incorporated
Viatrexx-Virus
Box of 1 X 100 mL bottle
For Oral and Topical Use
Expiry date: Lot #:
Manufactured for:
Viatrexx Bio Incorporated Newark, DE, USA, 19713
www.Viatrexx.com
Ingredients, homeopathic
See insert or www.viatrexx.com
Inactives: Alcohol 20%, Water 80%

NDC: 63776-570-17
Item: VPC0750
Viatrexx Bio Incorporated
Viatrexx-Virus
Box of 1 X 250 mL bottle
For Oral and Topical Use
Expiry date: Lot #:
Manufactured for:
Viatrexx Bio Incorporated Newark, DE, USA, 19713
www.Viatrexx.com
Ingredients, homeopathic
See insert or www.viatrexx.com
Inactives: Alcohol 20%, Water 80%